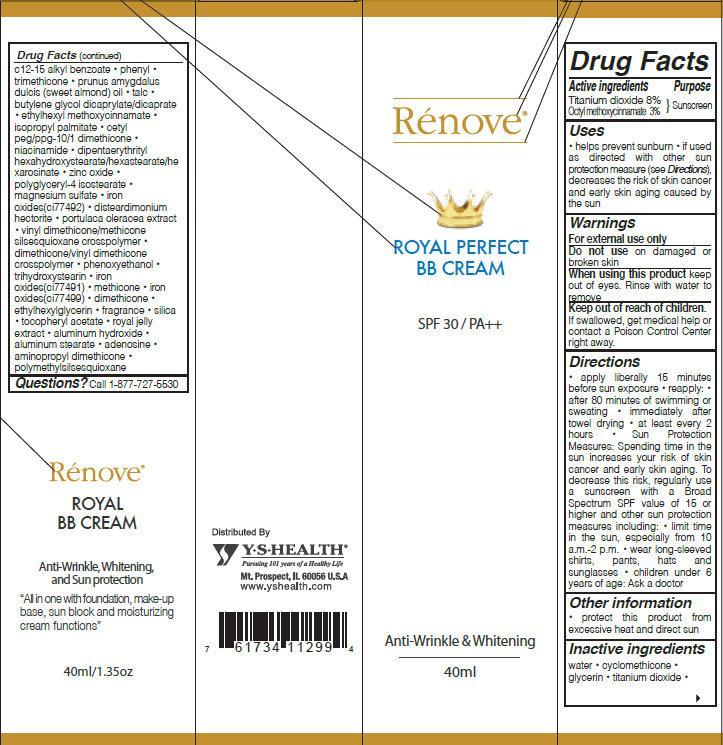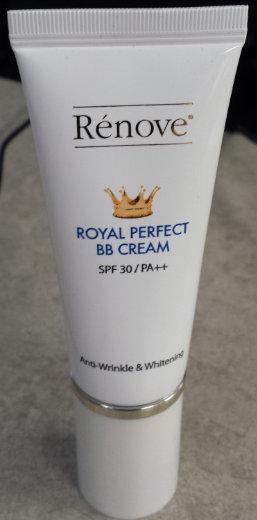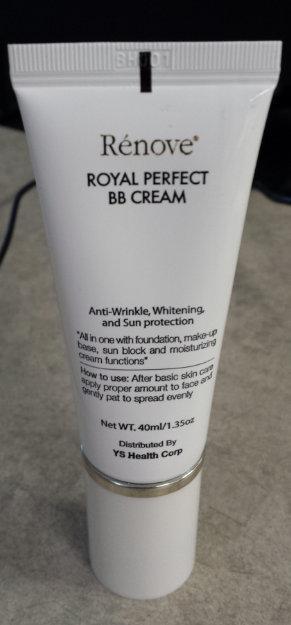 DRUG LABEL: Renove ROYAL PERFECT BB SPF 30
NDC: 60782-000 | Form: CREAM
Manufacturer: YS Health Corp.
Category: otc | Type: HUMAN OTC DRUG LABEL
Date: 20131003

ACTIVE INGREDIENTS: TITANIUM DIOXIDE 80 mg/1 mL; OCTINOXATE 30 mg/1 mL
INACTIVE INGREDIENTS: WATER; CYCLOMETHICONE; GLYCERIN; ALKYL (C12-15) BENZOATE; PHENYL TRIMETHICONE; ALMOND OIL; TALC; BUTYLENE GLYCOL DICAPRYLATE/DICAPRATE; ISOPROPYL PALMITATE; NIACINAMIDE; ZINC OXIDE; POLYGLYCERYL-4 ISOSTEARATE; MAGNESIUM SULFATE; FERRIC OXIDE YELLOW; DISTEARDIMONIUM HECTORITE; PURSLANE; PHENOXYETHANOL; TRIHYDROXYSTEARIN; FERRIC OXIDE RED; FERROSOFERRIC OXIDE; DIMETHICONE; ETHYLHEXYLGLYCERIN; .ALPHA.-TOCOPHEROL ACETATE; ALUMINUM HYDROXIDE; ALUMINUM STEARATE; ADENOSINE

Renove ROYAL PERFECT BB Cream SPF 30

Active ingredients

Titanium dioxide 8%
Octyl methoxycinnamate 3%

Purpose

Sunscreen

Uses

- helps prevent sunburn
- if used as directed with other sun protection measure (see Directions), decreases the risk of skin cancer and early skin aging caused by the sun

Warnings

For external use only

DO NOT USE

on damaged or broken skin

When using this product

keep out of eyes. Rinse with water to remove

Keep out of reach of children

If swallowed, get medical help or contact a Poison Control Center right away.

Directions

- apply liberally 15 minutes before sun exposure
- reapply:
-
  - after 80 minutes of swimming or sweating
  - immediately after towel drying
  - at least every 2 hours
- Sun Protection Measures: Spending time in the sun increases your risk of skin cancer and early skin aging. To decrease this risk, regularly use a sunscreen with a Broad Spectrum SPF value of 15 or higher and other sun protection measures including:
-
  - limit time in the sun, especially from 10 a.m. - 2 p.m.
  - wear long-sleeved shirts, pants, hats and sunglasses
- Children under 6 years of age: Ask a doctor

Other information

- protect this product from excessive heat and direct sun

Inactive ingredients

water, cyclomethicone, glycerin, titanium dioxide, c12-15 alkyl benzoate, phenyl trimethicone, prunus amygdalus dulcis (sweet almond) oil, talc, butylene glycol dicaprylate/dicaprate , ethylhexyl methoxycinnamate, isopropyl palmitate, cetyl peg/ppg-10/1 dimethicone, niacinamide, dipentaerythrityl hexahydroxystearate/hexastearate/hexarosinate, zinc oxide, polyglyceryl-4 isostearate, magnesium sulfate, iron oxides(ci77492), disteardimonium hectorite, portulaca oleracea extract, vinyl dimethicone/methicone silsesquioxane crosspolymer, dimethicone/vinyl dimethicone crosspolymer, phenoxyethanol, trihydroxystearin, iron oxides(ci77491), methicone, iron oxides(ci77499), dimethicone, ethylhexylglycerin, fragrance, silica, tocopheryl acetate , royal jelly extract, , aluminum hydroxide, aluminum stearate, adenosine, aminopropyl dimethicone, polymethylsilsesquioxane

Questions?

Call 1-877-727-5530